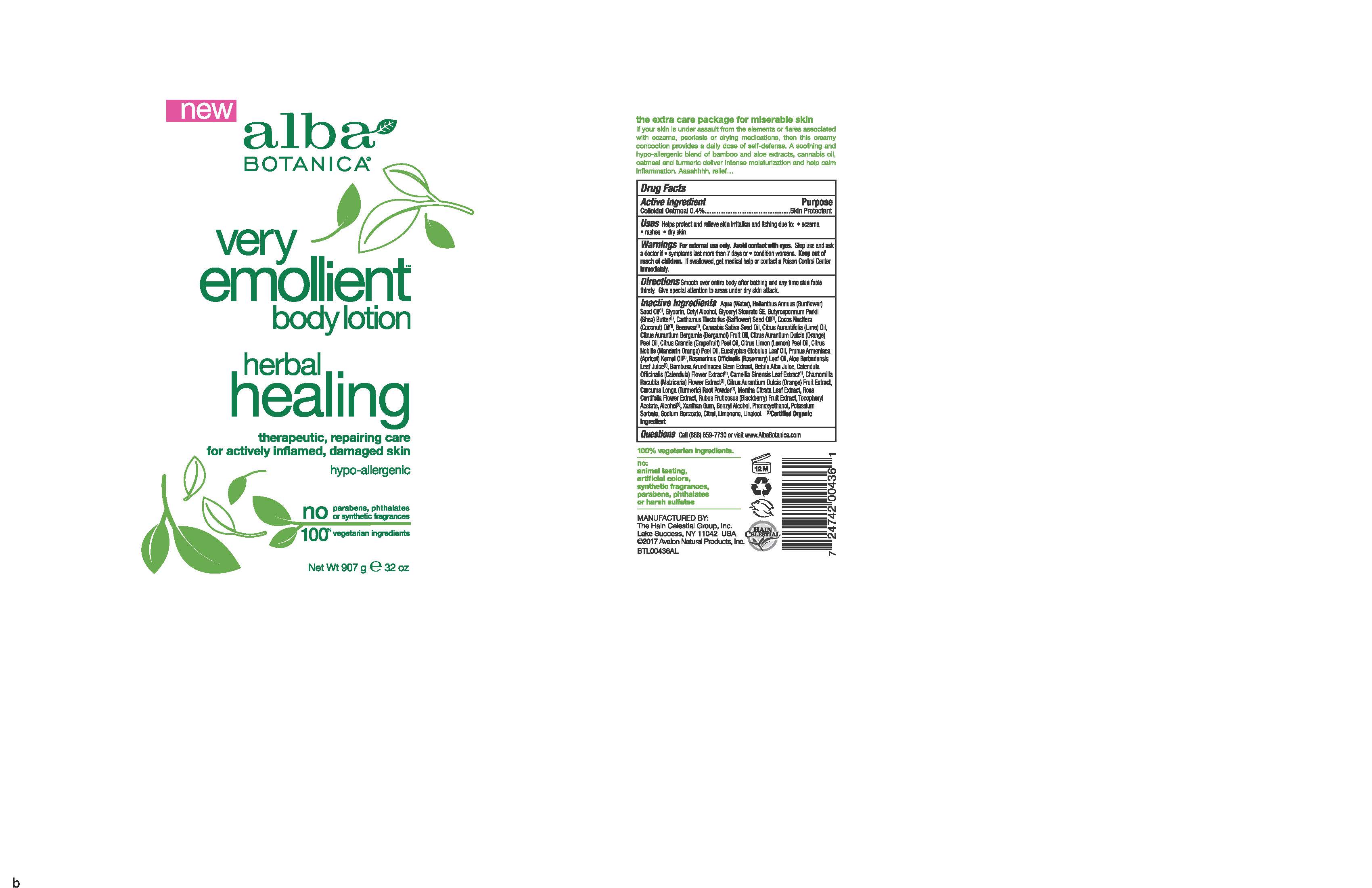 DRUG LABEL: AL0043600 Alba Botanica VE Herbal Healing Body
NDC: 61995-2436 | Form: LOTION
Manufacturer: The Hain Celestial Group, Inc.
Category: otc | Type: HUMAN OTC DRUG LABEL
Date: 20251210

ACTIVE INGREDIENTS: OATMEAL 0.4 g/100 g
INACTIVE INGREDIENTS: MANDARIN OIL; EUCALYPTUS GLOBULUS LEAF; ROSEMARY OIL; BAMBUSA ARUNDINACEA STEM; ORANGE OIL; CANNABIS SATIVA SEED OIL; LIME OIL; BERGAMOT OIL; GRAPEFRUIT OIL; LEMON OIL; APRICOT KERNEL OIL; GREEN TEA LEAF; RUBUS FRUTICOSUS WHOLE; COCONUT OIL; SAFFLOWER OIL; PHENOXYETHANOL; YELLOW WAX; CETYL ALCOHOL; ALCOHOL; BENZYL ALCOHOL; ALOE VERA LEAF; GLYCERIN; SUNFLOWER OIL; WATER; SHEA BUTTER; .ALPHA.-TOCOPHEROL ACETATE; GLYCERYL STEARATE SE; POTASSIUM SORBATE; CHAMOMILE; XANTHAN GUM; CALENDULA OFFICINALIS FLOWER; SODIUM BENZOATE; BIOTIN; BETULA PENDULA LEAF; TURMERIC; ROSA CENTIFOLIA FLOWER OIL; ANHYDROUS CITRIC ACID; SODIUM CITRATE; CITRUS AURANTIUM FRUIT OIL; MENTHA CITRATA LEAF

AL0043600 Alba Botanica VE Herbal Healing Body

Active Ingredient

Colloidal Oatmeal - 0.4%

DOSAGE AND ADMINISTRATION

Smooth over entire body after bathing and any time skin feels thirsty. Give special attention to areas under dry skin attack.

PURPOSE

Skin Protectant

WARNINGS

For external use only. Avoid contacts with eyes. Stop use and ask a doctor if symptoms last more than 7 days or condition worsens.

Keep out of reach of children. If swallowed get medical help or contact Poison Center immediately.

INACTIVE INGREDIENT

Water (Aqua), Helianthus Annuus (Sunflower) Seed Oil (1), Glycerin, Cetyl Alcohol, Glyceryl Stearate SE, Butyrospermum Parkii (Shea) Butter (1), Carthamus Tinctorius (Safflower) Seed Oil (1), Cocos Nucifera (Coconut) Oil (1), Beeswax (1), Cannabis Sativa Seed Oil, Citrus Aurantifolia (Lime) Oil, Citrus Aurantium Bergamia (Bergamot) Fruit Oil, Citrus Aurantium Dulcis (Orange) Peel Oil, Citrus Grandis (Grapefruit) Peel Oil, Citrus Limon (Lemon) Peel Oil, Citrus Nobilis (Mandarin Orange) Peel Oil, Eucalyptus Globulus Leaf Oil, Prunus Armeniaca (Apricot) Kernal Oil (1), Rosmarinus Officinalis (Rosemary) Leaf Oil, Aloe Barbadensis Leaf Juice (1), Bambusa Arundinacea Stem Extract, Betula Alba Juice, Calendula Officinalis Flower Extract (1), Camellia Sinensis Leaf Extract (1), Chamomilla Recutita (Matricaria) Flower Extract (1), Citrus Aurantium Dulcis (Orange) Fruit Extract, Curcuma Longa (Turmeric) Root Powder (1), Mentha Citrata Leaf Extract, Rosa Centifolia Flower Extract, Rubus Fruticosus (Blackberry) Fruit Extract, Biotin, Tocopheryl Acetate, Citric Acid, Sodium Citrate, Xanthan Gum, Alcohol (1), Benzyl Alcohol, Phenoxyethanol, Potassium Sorbate, Sodium Benzoate, Citral, Limonene, Linalool.

(1) Certified Organic Ingredient

INDICATIONS AND USAGE

Helps protect and relieve skin irritation and iching due to eczema, rashes, dry skin.